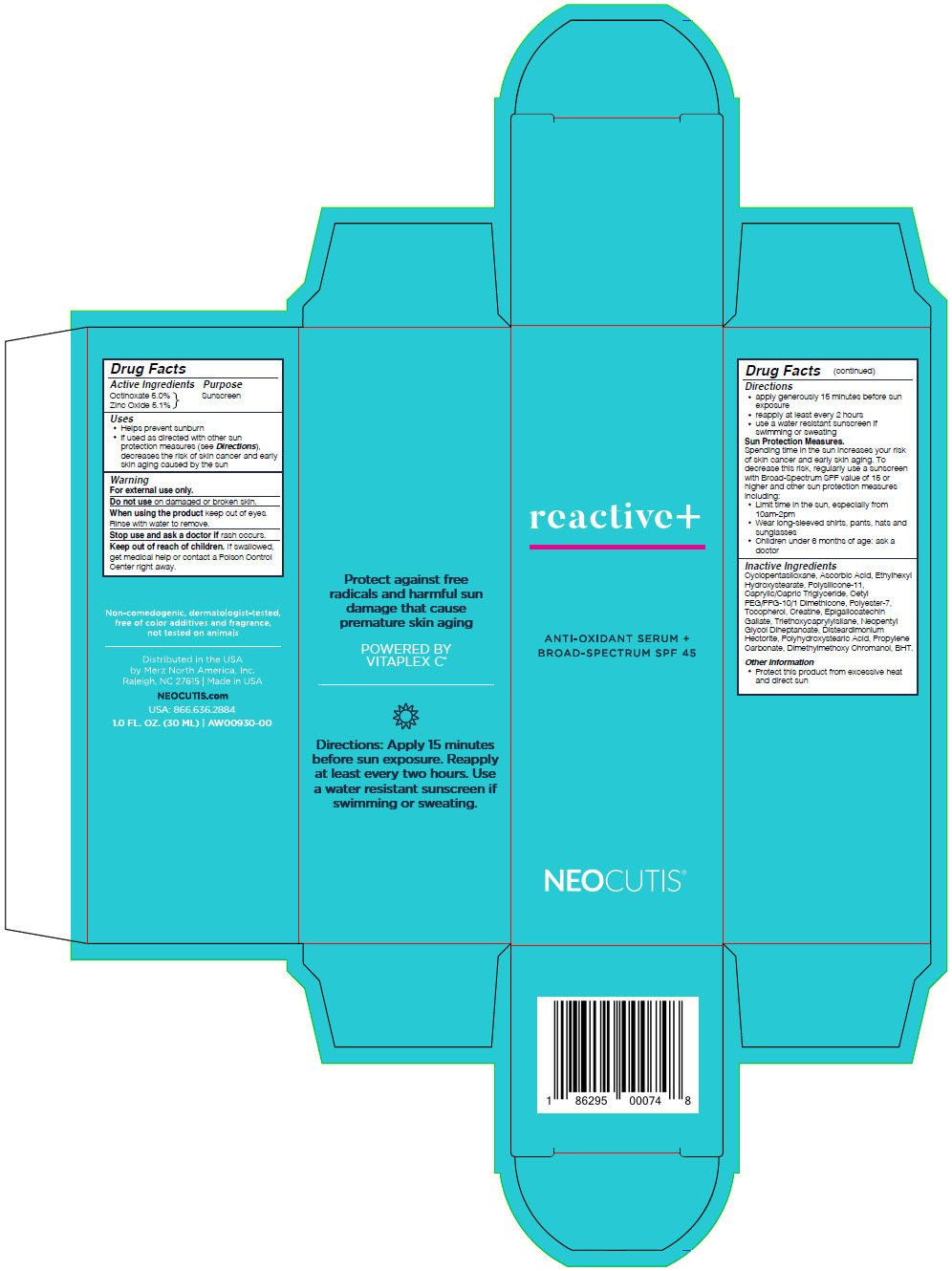 DRUG LABEL: Reactive Plus Anti-Oxidant Serum plus Broad-spectrum SPF 45
NDC: 46783-222 | Form: LOTION
Manufacturer: Merz North America, Inc
Category: otc | Type: HUMAN OTC DRUG LABEL
Date: 20241101

ACTIVE INGREDIENTS: OCTINOXATE 50 mg/1 mL; ZINC OXIDE 51 mg/1 mL
INACTIVE INGREDIENTS: CYCLOMETHICONE 5; ASCORBIC ACID; ETHYLHEXYL HYDROXYSTEARATE; POLYSILICONE-15; MEDIUM-CHAIN TRIGLYCERIDES; CETYL PEG/PPG-10/1 DIMETHICONE (HLB 2); POLYESTER-7; .ALPHA.-TOCOPHEROL ACETATE; CREATINE; EPIGALLOCATECHIN GALLATE; TRIETHOXYCAPRYLYLSILANE; NEOPENTYL GLYCOL DIHEPTANOATE; DISTEARDIMONIUM HECTORITE; POLYHYDROXYSTEARIC ACID (2300 MW); PROPYLENE CARBONATE; DIMETHYLMETHOXY CHROMANOL; BUTYLATED HYDROXYTOLUENE

Réactive+ Anti-Oxidant Serum plus Broad-spectrum SPF 45

Active Ingredients

Octinoxate 5.0%
Zinc Oxide 5.1%

Purpose

Sunscreen

Uses

- helps prevent sunburn
- if used as directed with other sun protection measures (see Directions), decreases the risk of skin cancer and early skin aging caused by the sun

WARNINGS

For external use only.

Do not use on damaged or broken skin.

When using this product keep out of eyes. Rinse with water to remove.

Stop use and ask a doctor if rash occurs.

Keep out of reach of children. If swallowed, get medical help or contact a Poison Control Center right away.

Directions

- apply generously 15 minutes before sun exposure
- reapply at least every 2 hours
- use a water resistant sunscreen if swimming or sweating
- Sun Protection Measures. Spending time in the sun increases your risk of skin cancer and early skin aging. To decrease this risk, regularly use a sunscreen with a Broad-Spectrum SPF value of 15 or higher and other sun protection measures including:
  - limit time in the sun, especially from 10am - 2pm
  - wear long-sleeved shirts, pants, hats, and sunglasses
- children under 6 months of age: ask a doctor

Inactive Ingredients

Cyclopentasiloxane, Ascorbic Acid, Ethylhexyl Hydroxystearate, Polysilicone-11, Caprylic/Capric Triglyceride, Cetyl PEG/PPG-10/1 Dimethicone, Polyester-7, Tocopherol, Creatine, Epigallocatechin Gallate, Triethoxycaprylylsilane, Neopentyl Glycol Diheptanoate, Disteardimonium Hectorite, Polyhydroxystearic Acid, Propylene Carbonate, Dimethylmethoxy Chromanol, BHT

Other Information

- protect the product in this container from excessive heat and direct sun

Questions?

1.844.469.6379

PRINCIPAL DISPLAY PANEL - 30 ML Bottle Carton

reactive+

ANTI-OXIDANT SERUM +
BROAD-SPECTRUM SPF 45

NEOCUTIS®